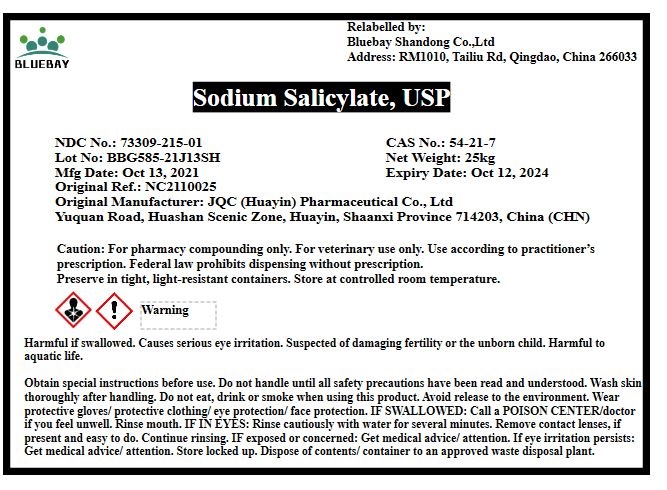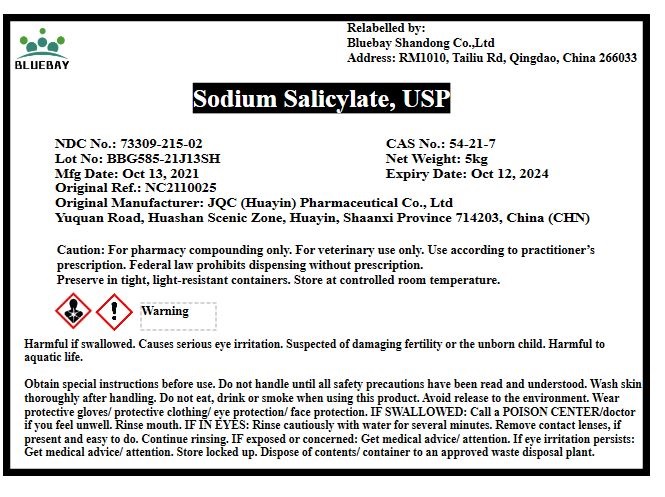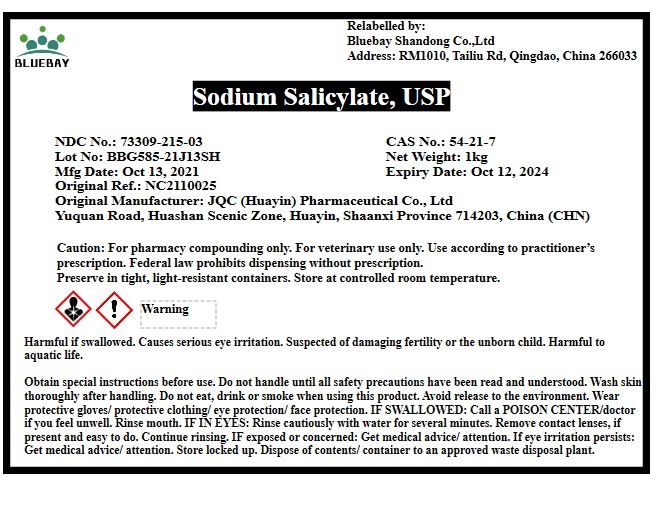 DRUG LABEL: Sodium Salicylate
NDC: 73309-215 | Form: POWDER
Manufacturer: BLUEBAY SHANDONG CO.,LTD
Category: other | Type: BULK INGREDIENT
Date: 20211108

ACTIVE INGREDIENTS: Sodium Salicylate 1 kg/1 kg

Sodium Salicylate